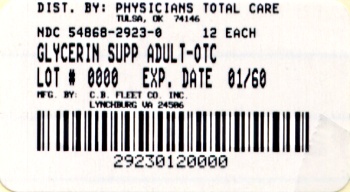 DRUG LABEL: Glycerin
NDC: 54868-2923 | Form: SUPPOSITORY
Manufacturer: Physicians Total Care, Inc.
Category: otc | Type: HUMAN OTC DRUG LABEL
Date: 20111214

ACTIVE INGREDIENTS: Glycerin 2 g/1 1
INACTIVE INGREDIENTS: EDETATE DISODIUM; WATER; SODIUM HYDROXIDE; STEARIC ACID

Drug Facts

Active Ingredient (in each suppository)

Glycerin 2 g.................Hyperosmotic Laxative

Use

For relief of occasional constipation.

Warnings

For rectal use only.
May cause rectal discomfort or a burning sensation.

Ask a doctor before using any laxative if you have

- abdominal pain, nausea or vomiting
- a sudden change in bowel habits lasting more than 2 weeks
- already used a laxative for more than 1 week

Stop use and consult a doctor if you have

- rectal bleeding
- no bowel movement after using product

These symptoms may indicate a serious condition.

Keep out of reach of children

If swallowed, get medical help or contact a Poison Control Center right away.

Directions

Single daily dosage

adults and children 6 years and over | 1 suppository, or as directed by a doctor
children 2 to under 6 years | use Pedia-Lax Glycerin Suppositories
children under 2 years | ask a doctor

Insert suppository well up into rectum. Suppository need not melt completely to produce laxative action.

Other Information

- This product generally produces a bowel movement in 1/4 to 1 hour.
- Store container tightly closed.
- Keep away from excessive heat.
- MOUTH OF JAR SEALED FOR SAFETY. IF FOIL IMPRINTED WITH GREEN FLEET EMBLEM IS BROKEN OR MISSING, DO NOT USE.

Inactive Ingredients

edetate disodium, purified water, sodium hydroxide, stearic acid

Questions?

1-866-255-6960 or www.fleetlabs.com

PRINCIPAL DISPLAY PANEL

Glycerin Suppositories laxative
12 Adult Suppositories
NDC 54868-2923-0

Additional barcode label appied by:
Physicians Total Care, Inc.
Tulsa, Oklahoma 74146